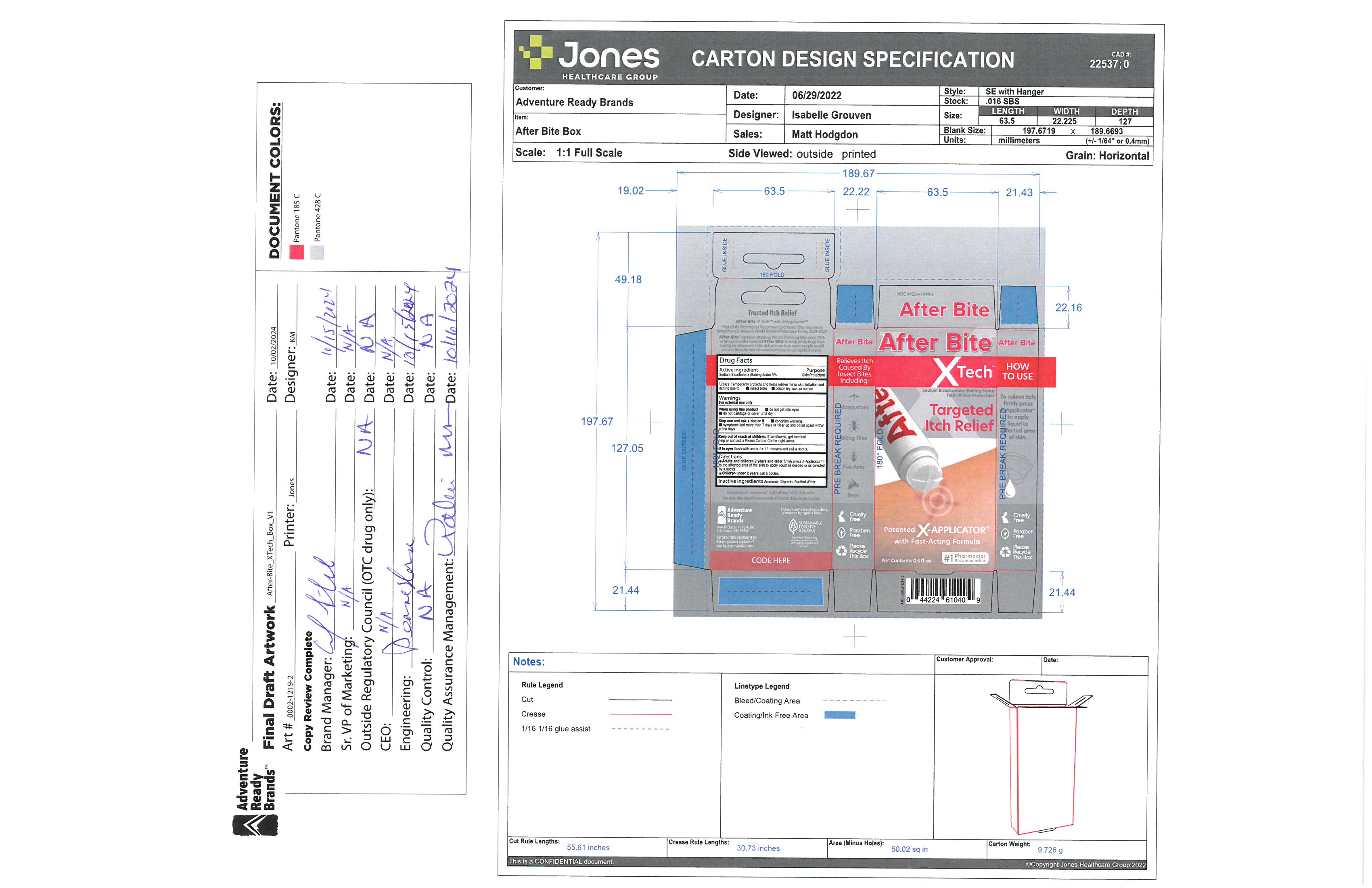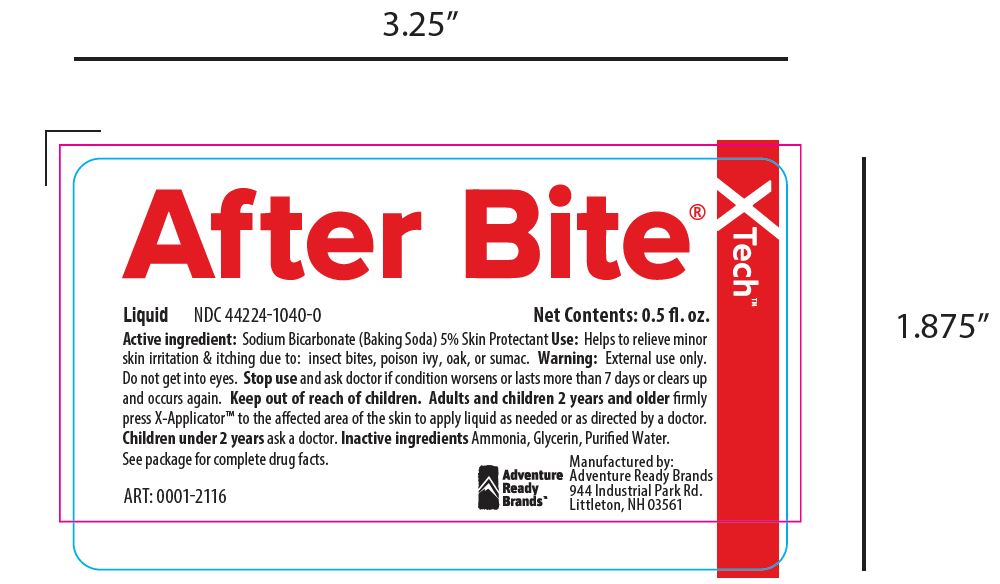 DRUG LABEL: After Bite X Tech
NDC: 44224-1040 | Form: LIQUID
Manufacturer: Adventure Ready Brands
Category: otc | Type: HUMAN OTC DRUG LABEL
Date: 20251117

ACTIVE INGREDIENTS: SODIUM BICARBONATE 50 mg/1000 mL
INACTIVE INGREDIENTS: WATER; AMMONIA; GLYCERIN

After Bite X Tech

Active Ingredient

Sodium Bicarbonate (Baking Soda) 5%

Purpose

Skin Protectant

Uses

Temporarily protects and helps relieve minor skin irritation and itching due to

- insect bites
- poison ivy, oak, or sumac

Warnings

For external use only

When using this product

- do not get into eyes
- do not bandage or cover until dry

Stop use and ask a doctor if

- condition worsens
- symptoms last more than 7 days or clear up and occur again within a few days

Keep out of reach of children

If swallowed, get medical help or contact a Poison Control Center right away.

If in eyes

flush with water for 15 minutes and call a doctor.

Directions

- Adults and children 2 years and older firmly press X-Applicator to the affected area of the skin to apply liquid as needed or as directed by a doctor.
- Children under 2 years ask a doctor.

Inactive Ingredients

Ammonia, Glycerin, Purified Water